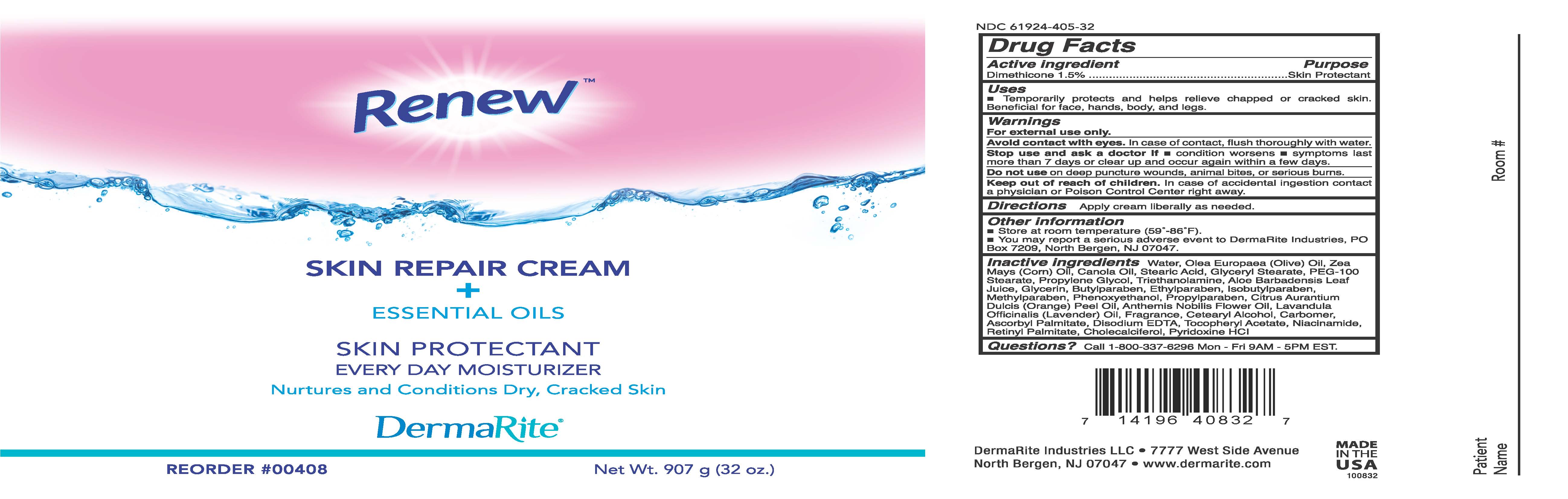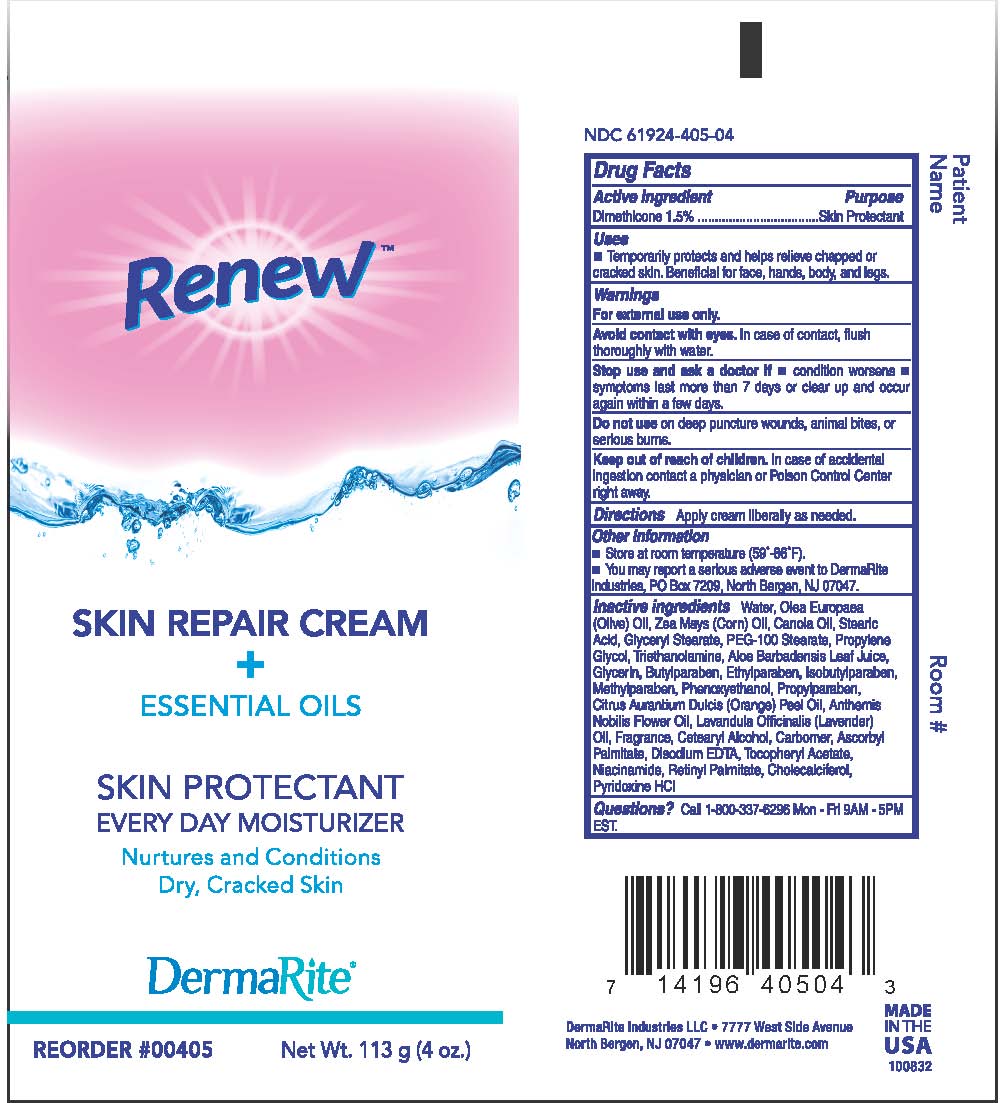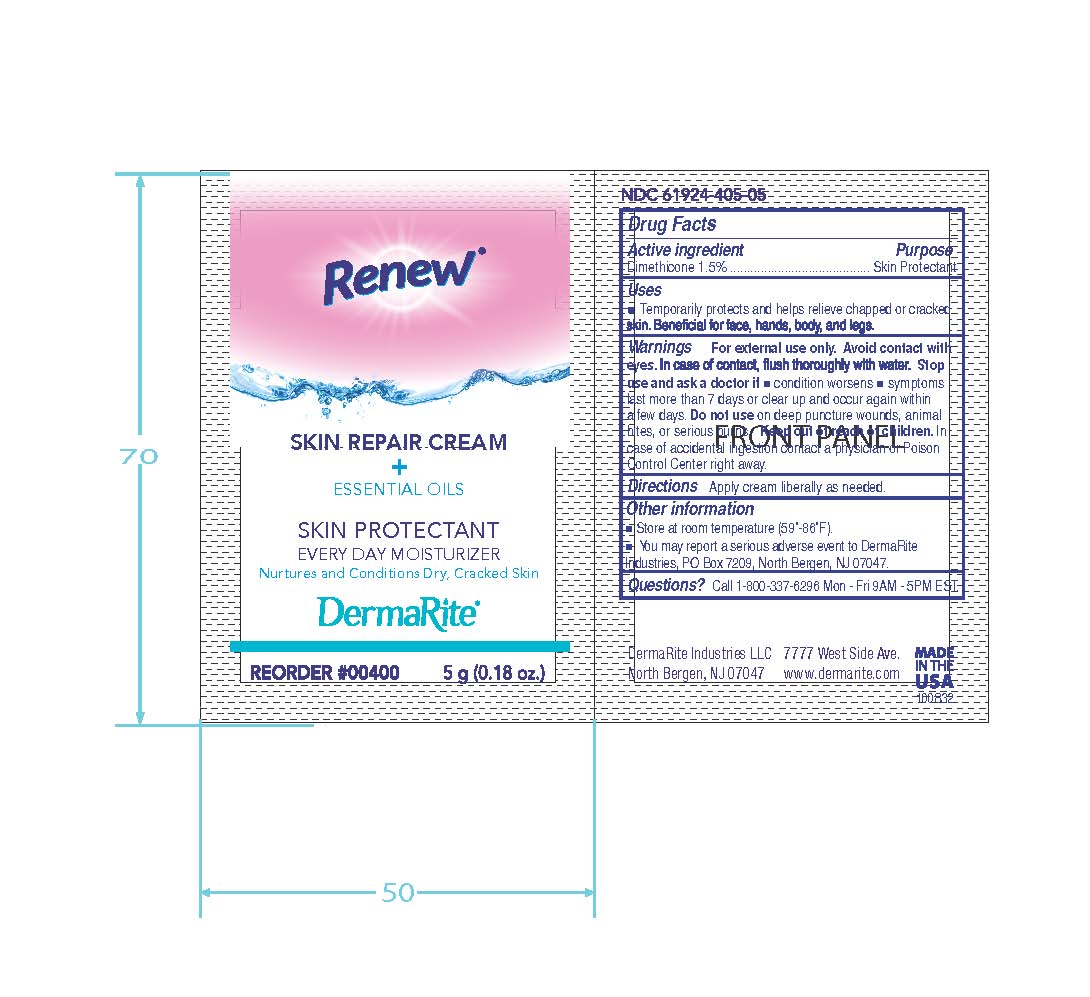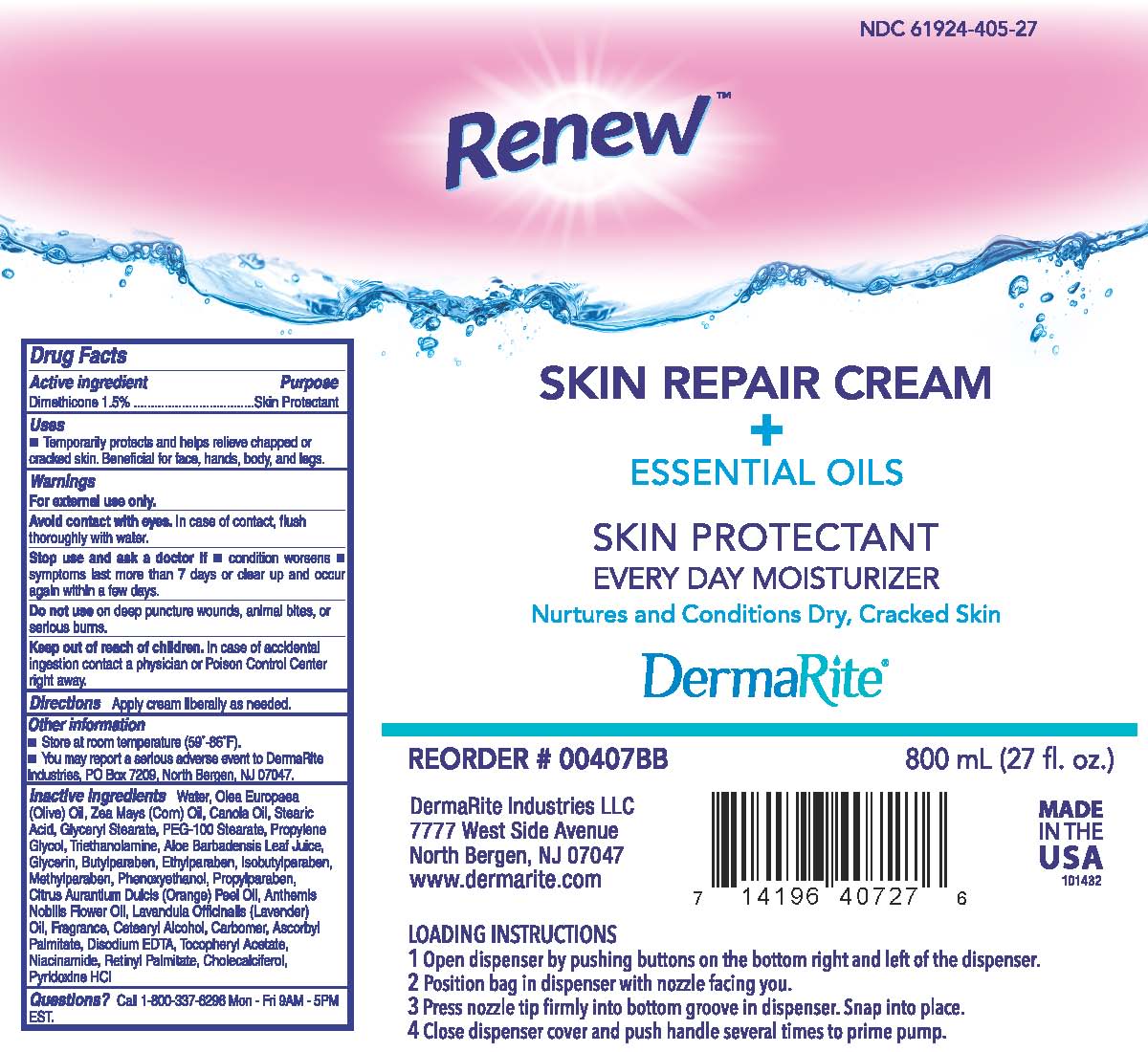 DRUG LABEL: RENEW SKIN REPAIR
NDC: 61924-405 | Form: CREAM
Manufacturer: Dermarite Industries LLC
Category: otc | Type: HUMAN OTC DRUG LABEL
Date: 20241205

ACTIVE INGREDIENTS: DIMETHICONE 0.015 g/100 g
INACTIVE INGREDIENTS: ALOE VERA LEAF; ASCORBYL PALMITATE; BUTYLPARABEN; CANOLA OIL; CARBOMER 940; CETOSTEARYL ALCOHOL; CHOLECALCIFEROL; ETHYLPARABEN; GLYCERIN; GLYCERYL MONOSTEARATE; ISOBUTYLPARABEN; METHYLPARABEN; NIACINAMIDE; OLIVE OIL; PEG-100 STEARATE; PHENOXYETHANOL; PROPYLENE GLYCOL; PROPYLPARABEN; PYRIDOXINE HYDROCHLORIDE; VITAMIN A PALMITATE; STEARIC ACID; .ALPHA.-TOCOPHEROL ACETATE; TROLAMINE; EDETATE DISODIUM; WATER; CORN OIL

DRUG LISTING: RENEW SKIN REPAIR CREAM

Active Ingredient:

Dimethicone 1.5%

Purpose:

Skin Protectant

Uses:

Temporarily protects and helps relieve chapped or cracked skin. Benificial for face, hands, body, and legs.

Warnings:

- For external use only.
- Avoid contact with eyes. In case of contact, flush thoroughly with water.
- Stop use and ask a doctor if condition worsens or does not improve within 7 days and if symptoms clear up and occur again within a few days.
- Do not use on deep or punctured wounds, animal bites, or serius burns.

Warnings:

- Keep out of reach of children. In case of accidental ingestion contact physician or Poison Control Center right away.

Directions:

Apply cream liberally as needed.

Other Information:

- Store at room temperature (59o- 86oF)
- You may report a serious adverse event to DermaRite Industries, PO Box 7209, North Bergen, NJ 07047

Inactive Infredients:

Water, Olea Europaea(Olive) Oil, Zea Mays (Corn) Oil, Canola Oil, Stearic Acid, glyceryl Stearate, PEG-100 Stearate, Propylene Glycol, Triethanolamine, Aloe Barbadensis Leaf Juice, Glycerin, Butylparaben, Ethylparaben, Isobutylparaben, methylparaben, Phenoxyethanol, propylparaben, Citrus Aurantium Dulcis (orange) Peel Oil, Anthemis Nobilis Flower Oil, Lavandula Officinalis (lavender) Oil, Fragrance, Cetearyl Alcohol, Carbomer, Ascorbyl Palmitate, Disodium EDTA, Tocopheryl Acetate, Niacinamide, Retinyl Palmitate, Cholecalciferol, Pyridoxine HCL

Questions?

Call 1-800-337-6296 Mon-Fri 9AM-5PM EST.